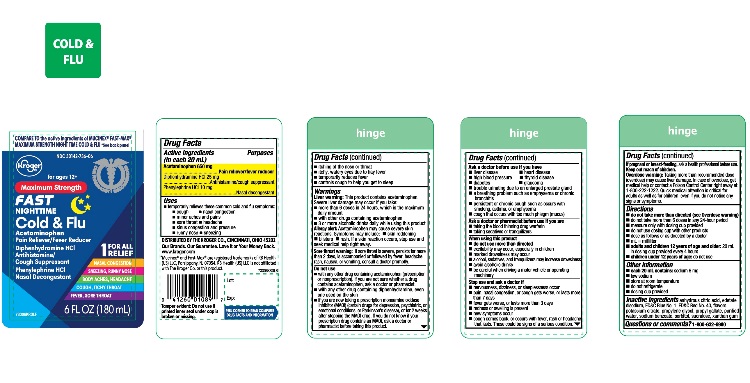 DRUG LABEL: Maximum Strength Nighttime Cold and Flu
NDC: 30142-736 | Form: LIQUID
Manufacturer: THE KROGER CO
Category: otc | Type: HUMAN OTC DRUG LABEL
Date: 20250812

ACTIVE INGREDIENTS: ACETAMINOPHEN 650 mg/20 mL; DIPHENHYDRAMINE HYDROCHLORIDE 25 mg/20 mL; PHENYLEPHRINE HYDROCHLORIDE 10 mg/20 mL
INACTIVE INGREDIENTS: ANHYDROUS CITRIC ACID; EDETATE DISODIUM; FD&C BLUE NO. 1; FD&C RED NO. 40; POTASSIUM CITRATE; PROPYLENE GLYCOL; PROPYL GALLATE; WATER; SODIUM BENZOATE; SORBITOL; SUCRALOSE; XANTHAN GUM

Maximum Strength Nighttime Cold and Flu 6 fl oz. (180 mL)

Drug Facts

ACTIVE INGREDIENT

PURPOSE

Active ingredients (in each 20 mL) | Purposes
Acetaminophen 650 mg | Pain reliever/fever reducer
Diphenhydramine HCl 25 mg | Antihistamine/cough suppressant
Phenylephrine HCl 10 mg | Nasal decongestant

Uses

- temporarily relieves these common cold and flu symptoms:
  - cough
  - nasal congestion
  - minor aches and pains
  - sore throat
  - headache
  - runny nose
  - sneezing
- temporarily reduces fever
- controls cough to help you get to sleep

Warnings

Liver Warning:

This product contains acetaminophen. Severe liver damage may occur if you take:

- more than 6 doses in 24 hours, which is the maximum daily amount
- with other drugs containing acetaminophen
- 3 or more alcoholic drinks daily while using this product

Allergy alert:Acetaminophen may cause severe skin reactions .Symptoms may include:

- Skin reddening
- Blisters
- rash
- If a skin reaction occurs, stop use and seek medical help right away.

Sore throat warning:if sore throat is severe, persists for more than 2 days, is accompanied or followed by fever, headache, rash, nausea, or vomiting, consult a doctor promptly.

Do not use

- with any other drug containing acetaminophen (prescription or nonprescription). If you are not sure whether a drug contains acetaminophen, ask a doctor or pharmacist.
- with any other drug containing diphenhydramine, even one used on the skin
- if you are now taking a prescription monoamine oxidase inhibitor (MAOI) (certain drugs for depression, psychiatric, or emotional conditions, or Parkinson's disease), or for 2 weeks after stopping the MAOI drug. If you do not know if your prescription drug contains an MAOI, ask a doctor or pharmacist before taking this product.

Ask a doctor before use if you have

- liver disease
- heart disease
- high blood pressure
- thyroid disease
- diabetes
- trouble urinating due to an enlarged prostate gland
- glaucoma
- a breathing problem such as emphysema or chronic bronchitis
- persistent or chronic cough such as occurs with smoking, asthma, chronic bronchitis, or emphysema

cough that occurs with too much phlegm (mucus)

Ask a doctor or pharmacist before use if

- you are taking the blood thinning drug warfarin
- taking sedatives or tranquilizers

When using this product

- do not use more than directed
- excitability may occur, especially in children
- marked drowsiness may occur
- alcohol, sedatives, and tranquilizers may increase drowsiness
- avoid alcoholic drinks

be careful when driving a motor vehicle or operating machinery

Stop use and ask a doctor if

- nervousness, dizziness, or sleeplessness occur
- pain, nasal congestion, or cough gets worse or lasts more than 7 days
- fever gets worse or lasts more than 3 days
- redness or swelling is present
- new symptoms occur
- cough comes back, or occurs with fever, rash, or headache that lasts. These could be signs of a serious condition.

PREGNANCY OR BREAST FEEDING

If pregnant or breast-feeding,ask a health professional before use.

Keep out of reach of children.

Overdose warning:

Taking more than the recommended dose (overdose) may cause liver damage. In case of overdose, get medical help or contact a Poison Control Center right away 1-800-222-1222. Quick medical attention is critical for adults as well as for children, even if you do not notice any signs or symptoms.

Directions

- do not take more than directed (see Overdose warning)
- do not take more than 6 doses in any 24-hour period
- measure only with dosing cup provided
- do not use dosing cup with other products
- dose as follows or as directed by a doctor
- mL= milliliter
- adults and children 12 years of age and older:20 mL in dosing cup provided every 4 hours
- children under 12 years of age:do not use

Other information

- each 20 mL contains:sodium 6 mg
- low sodium
- store at room temperature
- do not refrigerate
- dosing cup provided

Inactive ingredients

anhydrous citric acid, edetate disodium, FD&C blue #1, FD&C red #40, natural and artificial flavor, potassium citrate ,propylene glycol, propyl gallate, purified water, sodium benzoate, sorbitol, sucralose, xanthan gum.

Questions or comments?

1-888-287-1915

PRINCIPAL DISPLAY PANEL -

NDC# 30142-736-06

Compare to Mucinex®Fast-Max®Maximum Strength Might Time Cold & Flu Active Ingredients

Maximum Strength

Night Time Cold & Flu

- AcetaminophenPain Reliever/Fever Reducer
  Diphenhydramine HCl Antihistamine/Cough Suppressant
  Phenylephrine HCl Nasal Decongestant
- Relieves:

- Sore Throat; Itchy Throat-Cough
- Nasal Congestion – Sneezing & Runny Nose
- Headache – Body Pain

For Ages 12+

6 FL OZ (180 mL)

*This product is not manufactured or distributed by Reckitt Benckiser, the distributor of Mucinex®Fast- Max®Maximum Strength Nighttime Cold & Flu

Tamper evident: do not use if printed seal under cap is broken or missing.

‡Maximum Strength per 4 hour dose.

Distributed by: